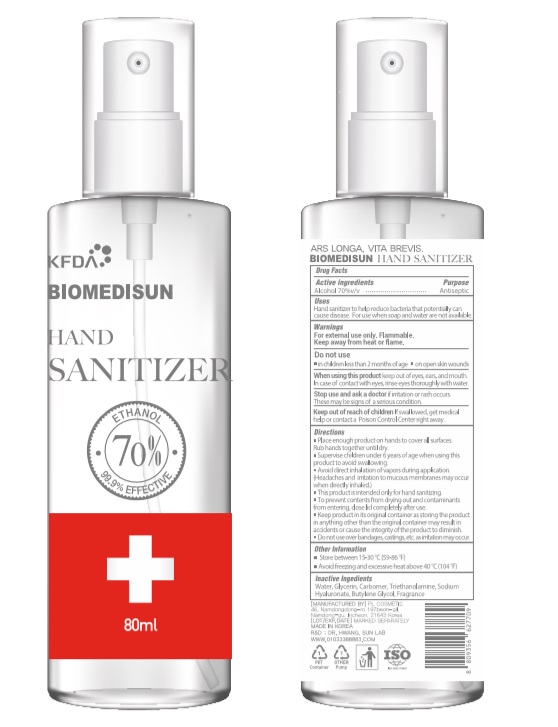 DRUG LABEL: BIOMEDISUN HAND SANITIZER
NDC: 74339-3870 | Form: SPRAY
Manufacturer: PL COSMETIC
Category: otc | Type: HUMAN OTC DRUG LABEL
Date: 20200424

ACTIVE INGREDIENTS: ALCOHOL 56 mL/80 mL
INACTIVE INGREDIENTS: GLYCERIN; CARBOMER HOMOPOLYMER, UNSPECIFIED TYPE; WATER; BUTYLENE GLYCOL; HYALURONATE SODIUM; TROLAMINE

[BIOMEDISUN] 80 ml SPRAY TYPE(Liquid form) 70: 74339-3870